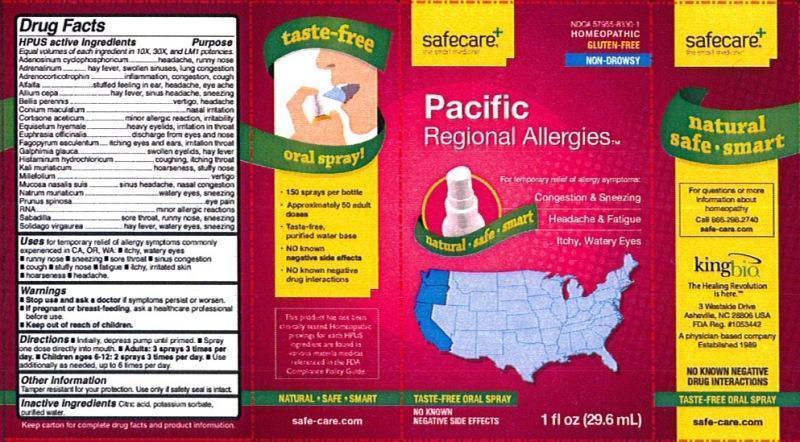 DRUG LABEL: Pacific Regional Allergies
NDC: 57955-8330 | Form: LIQUID
Manufacturer: King Bio Inc.
Category: homeopathic | Type: HUMAN OTC DRUG LABEL
Date: 20131202

ACTIVE INGREDIENTS: ADENOSINE CYCLIC PHOSPHATE 10 [hp_X]/29.6 mL; EPINEPHRINE 10 [hp_X]/29.6 mL; CORTICOTROPIN 10 [hp_X]/29.6 mL; ALFALFA 10 [hp_X]/29.6 mL; ONION 10 [hp_X]/29.6 mL; BELLIS PERENNIS 10 [hp_X]/29.6 mL; CONIUM MACULATUM FLOWERING TOP 10 [hp_X]/29.6 mL; CORTISONE ACETATE 10 [hp_X]/29.6 mL; EQUISETUM HYEMALE 10 [hp_X]/29.6 mL; EUPHRASIA STRICTA 10 [hp_X]/29.6 mL; FAGOPYRUM ESCULENTUM 10 [hp_X]/29.6 mL; GALPHIMIA GLAUCA FLOWERING TOP 10 [hp_X]/29.6 mL; HISTAMINE DIHYDROCHLORIDE 10 [hp_X]/29.6 mL; POTASSIUM CHLORIDE 10 [hp_X]/29.6 mL; ACHILLEA MILLEFOLIUM 10 [hp_X]/29.6 mL; SUS SCROFA NASAL MUCOSA 10 [hp_X]/29.6 mL; SODIUM CHLORIDE 10 [hp_X]/29.6 mL; PRUNUS SPINOSA FLOWER BUD 10 [hp_X]/29.6 mL; SACCHAROMYCES CEREVISIAE RNA 10 [hp_X]/29.6 mL; SCHOENOCAULON OFFICINALE SEED 10 [hp_X]/29.6 mL; SOLIDAGO VIRGAUREA FLOWERING TOP 10 [hp_X]/29.6 mL
INACTIVE INGREDIENTS: CITRIC ACID MONOHYDRATE; POTASSIUM SORBATE; WATER

Pacific Regional Allergies™

Drug Facts

____________________________________________________________________________________________________________

Equal volumes of each ingredient in 10X, 30X, and LM1 potencies.

HPUS active ingredients: Adenosinum cyclophosphoricum, Adrenalinum, Adrenocorticotrophin, Alfalfa, Allium cepa, Bellis perennis, Conium maculatum, Cortisone aceticum, Equisetum hyemale, Euphrasia officinalis, Fagopyrum esculentum, Galphimia glauca, Histaminum hydrochloricum, Kali muriaticum, Millefolium, Mucosa nasalis suis, Natrum muriaticum, Prunus spinosa, RNA, Sabadilla, Solidago virgaurea.

INDICATIONS AND USAGE

Uses for temporary relief of allergy symptoms commonly experienced in CA, OR, WA:

- itchy, watery eyes
- runny nose
- sneezing
- sore throat
- sinus congestion
- cough
- stuffy nose
- fatigue
- itchy, irritated skin
- hoarseness
- headache

Warnings

- Stop use and ask a doctor if symptoms persist or worsen.
- If pregnant or breast-feeding, ask a healthcare professional before use.

- Keep out of reach of children.

Directions:

- Initially, depress pump until primed.
- Spray one dose directly into mouth.
- Adults: 3 sprays 3 times per day.
- Children ages 6-12: 2 sprays 3 times per day.
- Use additionally as needed, up to 6 times per day.

OTHER SAFETY INFORMATION

Tamper resistant for your protection. Use only if safety seal is intact.

Inactive Ingredients: Citric acid, potassium sorbate, purified water.

Drug Facts

__________________________________________________________________________________________________________________

HPUS active ingredients Purpose

Equal volumes of each ingredient in 10X, 30X, and LM1 potencies.

Adenosinum cyclophosphoricum............................................headache, runny nose

Adrenalinum.......................................................................hay fever, swollen sinuses, lung congestion

Adrenocorticotrophin............................................................inflammation, congestion, cough

Alfalfa................................................................................stuffed feeling in ear, headache, eye ache

Allium cepa.........................................................................hay fever, sinus headache, sneezing

Bellis perennis.....................................................................vertigo, headache

Conium maculatum..............................................................nasal irritation

Cortisone aceticum..............................................................minor allergic reaction, irritability

Equisetum hyemale.............................................................heavy eyelids, irritation in throat

Euphrasia officinalis.............................................................discharge from eyes and nose

Fagopyrum esculentum........................................................itching eyes and ears, irritation throat

Galphimia glauca................................................................swollen eyelids, hay fever

Histaminum hydrochloricum.................................................coughing, itching throat

Kali muriaticum..................................................................hoarseness, stuffy nose

Millefolium.........................................................................vertigo

Mucosa nasalis suis.............................................................sinus headache, nasal congestion

Natrum muriaticum.............................................................watery eyes, sneezing

Prunus spinosa...................................................................eye pain

RNA..................................................................................minor allergic reactions

Sabadilla...........................................................................sore throat, runny nose, sneezing

Solidago virgaurea...............................................................hay fever, watery eyes, sneezing